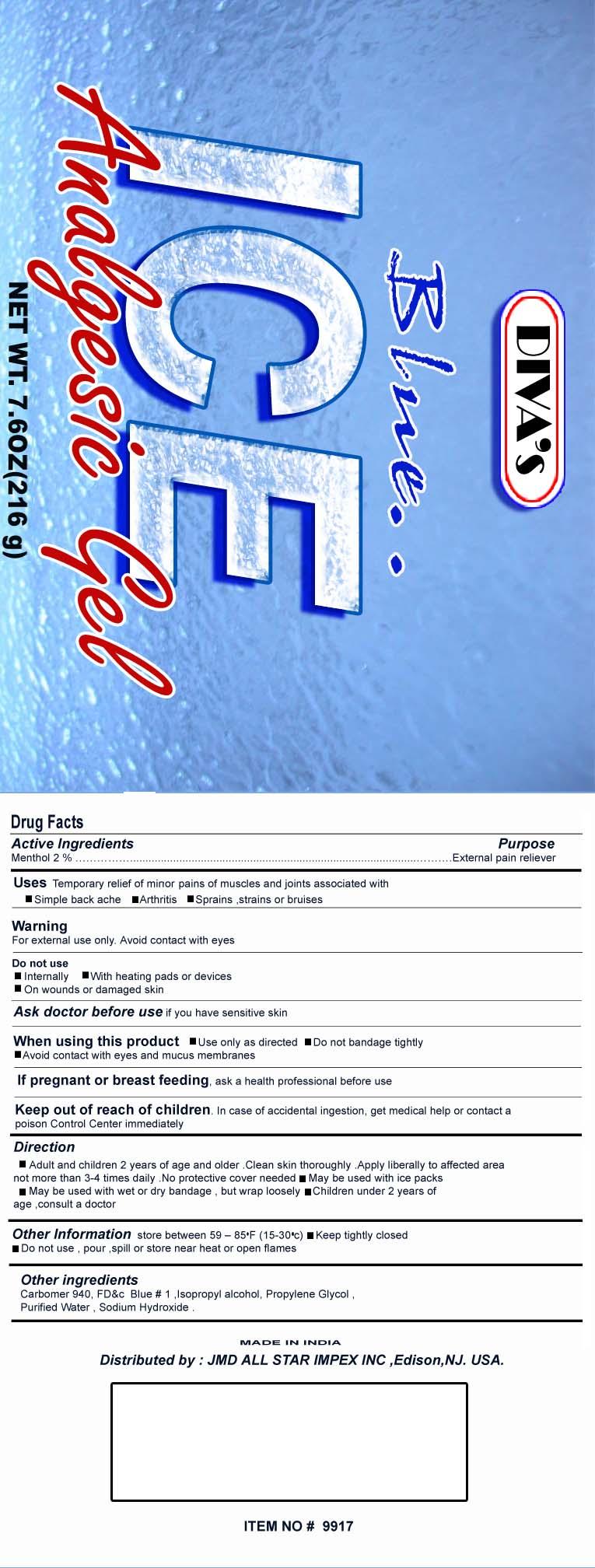 DRUG LABEL: Blue Ice 
NDC: 51444-002 | Form: GEL
Manufacturer: JMD All Star Impex Inc
Category: otc | Type: HUMAN OTC DRUG LABEL
Date: 20100530

ACTIVE INGREDIENTS: Menthol 2 g/100 g
INACTIVE INGREDIENTS: CARBOMER HOMOPOLYMER TYPE C; FD&C BLUE NO. 1; ISOPROPYL ALCOHOL; PROPYLENE GLYCOL; WATER; SODIUM HYDROXIDE

Active Ingredient
Menthol 2.0%

Purpose
External pain reliever

Uses
Temporary relief of minor pains of muscles and joints associated with

- Simple back ache
- Arthritis
- Sprains, strains or bruises

Warning
For external use only. Avoid contact with eyes

Do not use

- Internally
- With heating pads or devices
- On wounds or damaged skin

Ask doctor before use if you have sensitive skin

When using this product

- Use only as directed
- Do not bandage tightly
- Avoid contact with eyes and mucus membranes

PREGNANCY OR BREAST FEEDING

If pregnant or breast feeding, ask a health professional before use

Keep out of reach of children. In case of accidental ingestion, get medical help or contact a Poison Control Center immediately

INDICATIONS AND USAGE

Direction

- Adult and children 2 years of age and older. Clean skin thoroughly. Apply liberally to affected area not more than 3-4 times daily. No protective cover needed.
- May be used with ice packs
- May be used with wet or dry bandage, but wrap loosely
- Children under 2 years of age, consult a doctor

Other Information store between 59-85F (15-30C)

- Keep tightly closed
- Do not use, pour, spill or store near heat or open flames

INACTIVE INGREDIENT

Other Ingredients Carbomer 940, FDC Blue No. 1, Isopropyl Alcohol, Propylene Glycol, Purified Water, Sodium Hydroxide,

Package Label